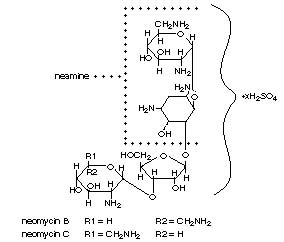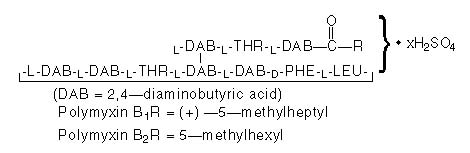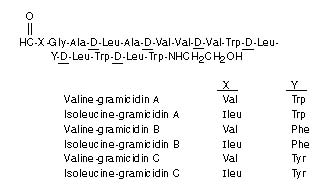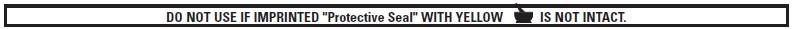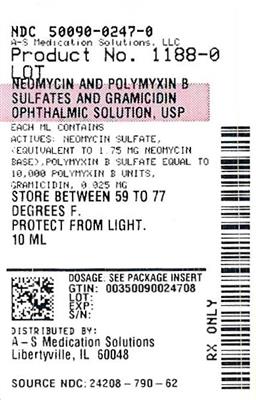 DRUG LABEL: NEOMYCIN AND POLYMYXIN B SULFATES AND GRAMICIDIN
NDC: 50090-0247 | Form: SOLUTION/ DROPS
Manufacturer: A-S Medication Solutions
Category: prescription | Type: HUMAN PRESCRIPTION DRUG LABEL
Date: 20260204

ACTIVE INGREDIENTS: NEOMYCIN SULFATE 1.75 mg/1 mL; POLYMYXIN B SULFATE 10000 [USP'U]/1 mL; GRAMICIDIN 0.025 mg/1 mL
INACTIVE INGREDIENTS: SODIUM CHLORIDE; DEHYDRATED ALCOHOL; POLOXAMER 188; PROPYLENE GLYCOL; AQUA; HYDROCHLORIC ACID; AMMONIA; THIMEROSAL 0.01 mg/1 mL

Neomycin and Polymyxin B Sulfates and Gramicidin Ophthalmic Solution, USP

(Sterile)

Rx only

DESCRIPTION

Neomycin and polymyxin B sulfates and gramicidin ophthalmic solution, USP is a sterile antimicrobial solution for ophthalmic use.

Each mL contains: Actives:neomycin sulfate, (equivalent to 1.75 mg neomycin base), polymyxin B sulfate equal to 10,000 polymyxin B units, gramicidin, 0.025 mg; Inactives:sodium chloride, alcohol (0.5%), Poloxamer 188, propylene glycol, purified water. Hydrochloric acid and/or ammonium hydroxide may be added to adjust pH (4.7-6.0).

Preservative:thimerosal 0.001%.

Neomycin Sulfate is the sulfate salt of neomycin B and C, which are produced by the growth of Streptomyces fradiaeWaksman (Fam. Streptomycetaceae). It has a potency equivalent of not less than 600 micrograms of neomycin base per milligram, calculated on an anhydrous basis.

The structural formulae are:

Polymyxin B Sulfate is the sulfate salt of polymyxin B1and B2which are produced by the growth of Bacillus polymyxa(Prazmowski) Migula (Fam. Bacillaceae). It has a potency of not less than 6,000 polymyxin B units per milligram, calculated on an anhydrous basis. The structural formulae are:

Gramicidin (also called gramicidin D) is a mixture of three pairs of antibacterial substances (Gramicidin A, B and C) produced by the growth of Bacillus brevisDubos (Fam. Bacillaceae). It has a potency of not less than 900 mcg of standard gramicidin per mg. The structural formulae are:

CLINICAL PHARMACOLOGY

A wide range of antibacterial action is provided by the overlapping spectra of neomycin, polymyxin B sulfate, and gramicidin.

Neomycin is bactericidal for many gram-positive and gram-negative organisms. It is an aminoglycoside antibiotic which inhibits protein synthesis by binding with ribosomal RNA and causing misreading of the bacterial genetic code.

Polymyxin B is bactericidal for a variety of gram-negative organisms. It increases the permeability of the bacterial cell membrane by interacting with the phospholipid components of the membrane.

Gramicidin is bactericidal for a variety of gram-positive organisms. It increases the permeability of the bacterial cell membrane to inorganic cations by forming a network of channels through the normal lipid bilayer of the membrane.

Microbiology:

Neomycin sulfate, polymyxin B sulfate, and gramicidin together are considered active against the following microorganisms: Staphylococcus aureus, streptococci, including Streptococcus pneumoniae, Escherichia coli, Haemophilus influenzae, Klebsiella-Enterobacterspecies, Neisseriaspecies, and Pseudomonas aeruginosa. The product does not provide adequate coverage against Serratia marcescens.

INDICATIONS AND USAGE

Neomycin and polymyxin B sulfates and gramicidin ophthalmic solution is indicated for the topical treatment of superficial infections of the external eye and its adnexa caused by susceptible bacteria. Such infections encompass conjunctivitis, keratitis and keratoconjunctivitis, blepharitis and blepharoconjunctivitis.

CONTRAINDICATIONS

This product is contraindicated in those persons who have shown hypersensitivity to any of its components.

WARNINGS

NOT FOR INJECTION INTO THE EYE. This product should never be directly introduced into the anterior chamber of the eye or injected subconjunctivally.

Topical antibiotics, particularly neomycin sulfate, may cause cutaneous sensitization. A precise incidence of hypersensitivity reactions (primarily skin rash) due to topical antibiotics is not known.

The manifestations of sensitization to topical antibiotics are usually itching, reddening and edema of the conjunctiva and eyelid. A sensitization reaction may manifest simply as a failure to heal. During long-term use of topical antibiotic products, periodic examination for such signs is advisable, and the patient should be told to discontinue the product if they are observed. Symptoms usually subside quickly on withdrawing the medication. Applications of products containing these ingredients should be avoided for the patient thereafter (see PRECAUTIONS: Error! Hyperlink reference not valid.).

PRECAUTIONS

General

GENERAL PRECAUTIONS

As with other antibiotic preparations, prolonged use of this product may result in overgrowth of nonsusceptible organisms including fungi. If superinfection occurs, appropriate measures should be initiated.

Bacterial resistance to this product may also develop. If purulent discharge, inflammation or pain becomes aggravated, the patient should discontinue use of the medication and consult a physician.

There have been reports of bacterial keratitis associated with the use of topical ophthalmic products in multiple-dose containers which have been inadvertently contaminated by patients, most of whom had a concurrent corneal disease or a disruption of the ocular epithelial surface (see PRECAUTIONS: Information for Patients).

Allergic cross-reactions may occur which could prevent the use of any or all of the following antibiotics for the treatment of future infections: kanamycin, paromomycin, streptomycin, and possibly gentamicin.

Information for Patients

Patients should be instructed to avoid allowing the tip of the dispensing container to contact the eye, eyelid, fingers, or any other surface. The use of this product by more than one person may spread infection.

Patients should also be instructed that ocular products, if handled improperly, can become contaminated by common bacteria known to cause ocular infections. Serious damage to the eye and subsequent loss of vision may result from using contaminated products (see PRECAUTIONS: Error! Hyperlink reference not valid.).

If the condition persists or gets worse, or if a rash or other allergic reaction develops, the patient should be advised to stop use and consult a physician. Do not use this product if you are allergic to any of the listed ingredients.

Keep tightly closed when not in use. Keep out of reach of children.

Carcinogenesis, Mutagenesis, Impairment of Fertility

Long-term studies in animals to evaluate carcinogenic or mutagenic potential have not been conducted with polymyxin B sulfate or gramicidin. Treatment of cultured lymphocytes in vitro with neomycin increased the frequency of chromosome aberrations at the highest concentration (80 mcg/mL) tested. However, the effects of neomycin on carcinogenesis and mutagenesis in humans are unknown.

Polymyxin B has been reported to impair the motility of equine sperm, but its effects on male or female fertility are unknown.

Pregnancy: Teratogenic Effects

Adequate animal reproductive studies have not been conducted with neomycin, polymyxin B, or gramicidin. It is also not known whether this product can cause fetal harm when administered to a pregnant woman or can affect reproduction capacity. This product should be given to a pregnant woman only if clearly needed.

Nursing Mothers

It is not known whether this drug is excreted in human milk. Because many drugs are excreted in human milk, caution should be exercised when this product is administered to a nursing woman.

Pediatric Use

Safety and effectiveness in pediatric patients have not been established.

ADVERSE REACTIONS

Adverse reactions have occurred with the anti-infective components of this product. The exact incidence is not known. Reactions occurring most often are allergic reactions including itching, swelling, and conjunctival erythema (see WARNINGS). More serious hypersensitivity reactions, including anaphylaxis, have been reported rarely.

Local irritation on instillation has also been reported.

To report SUSPECTED ADVERSE REACTIONS, contact Bausch & Lomb Incorporated at 1-800-553-5340 or FDA at 1-800-FDA-1088 or www.fda.gov/medwatch.

DOSAGE AND ADMINISTRATION

Instill one or two drops into the affected eye every 4 hours for 7 to 10 days. In severe infections, dosage may be increased to as much as two drops every hour.

HOW SUPPLIED

Product: 50090-0247

NDC: 50090-0247-0 10 mL in a BOTTLE, DROPPER / 1 in a CARTON

Distributed by:

Bausch & Lomb Americas Inc.
Bridgewater, NJ 08807 USA

Manufactured by:

Bausch & Lomb Incorporated

Tampa, FL 33637 USA
© 2022 Bausch & Lomb Incorporated or its affiliates

Revised: August 2022

9113405 (Folded)
9113505 (Flat)